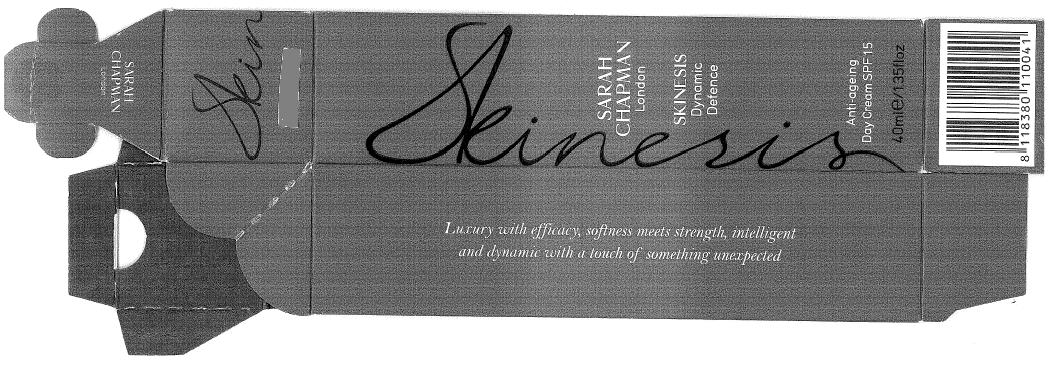 DRUG LABEL: SARAH CHAPMAN London SKINESIS Dynamic Defence  Anti-Ageing Day  SPF 15
NDC: 62742-4029 | Form: CREAM
Manufacturer: Allure Labs, Inc.
Category: otc | Type: HUMAN OTC DRUG LABEL
Date: 20100622

ACTIVE INGREDIENTS: OCTINOXATE 50 mg/1 mL; OCTISALATE 50 mg/1 mL; OXYBENZONE 30 mg/1 mL; AVOBENZONE 20 mg/1 mL

Drug Facts

ACTIVE INGREDIENTS:

1. OCTINOXATE (OCTYL METHOXYCINNAMATE) 5%

2. OCTISALATE (OCTYL SALICYLATE) 5%

3. OXYBENZONE (BENZOPHENONE-3) 3%

4. AVOBENZONE (1-4-TERT-BUTYLPHENYL-3-(4-METHOXYPHENYL) PROPANE-1,3-DIONE) 2%

INACTIVE INGREDIENTS:

PURIFIED WATER, C12 -15 ALKYL BENZOATE, DIMETHICONE, CAPRYLIC / CAPRIC TRIGLYCERIDE, GLYCERINE, RUMEX OCCIDENTALIS EXTRACT, C14-22 ALCOHOLS, CETYL ALCOHOL, CRAMBE ABYSSINICA SEED OIL, GLYCERYL STEARATE, PEG-100 STEARATE, TETRAHEXYLDECYL ASCORBATE, ARCTOSTAPHYLOW UVA URSI LEAF EXTRACT, TEPRENONE, PALMITOYL TETRAPEPTIDE 7, HYDROXYETHYL ACRYLATE / SODIUM ACRYOYDIMETHYL TAURATE COPOLYMER, BUTELENE GLYCOL, SQUALANE, C 12 - 20 ALKYL GLUCOSIDES, POLYSORBATE 60, SODIUM PCA, LECITHIN, PLANKTON EXTRACT, MANGIFERA INDICA SEED BUTTER, BUTYROSPERMUM PARKII, NYLON 12, YEAST POLYSACCHARADIES, PHYLLANTHUS EMBLICA FRUIT EXTRACT, RETINYL PALMITATE, UBIQUINONE, TOCOPHEROL ACETATE, PHENOXYEHTHANOL, CAPRYLYL GLYCOL, ETHYLHEXYLGLYCERINE, HEXYLENE GLYCOL, CERUS DEODORA WOOD OIL, IRIS FLORENTINA ROOT EXTRACT, ROSA CANINA FLOWER EXTRACT, JASMINUM OFFICINALE FLOWER EXTRACT, DISODIUM EDTA, HYDROXYDECYL UBIQUINONE, HYACINTHUS ORIENTALIS FLOWER EXTRACT, JASMINUM GRANDIFLORUM FLOWER WAX, SANTALUM ALBUM OIL, DIETHYLHEXYL SYRINGYLDENE MALONATE, PELARGONIUM GRAVEOLENS FLOWER OIL, ROSA DAMASCENA FLOWER OIL.

PACKAGE LABEL

Image of Carton:

SARAH CHAPMAN London

SKINESIS Dynamic Defence

Anti-ageing Day Cream SPF 15

40ml/1.35floz